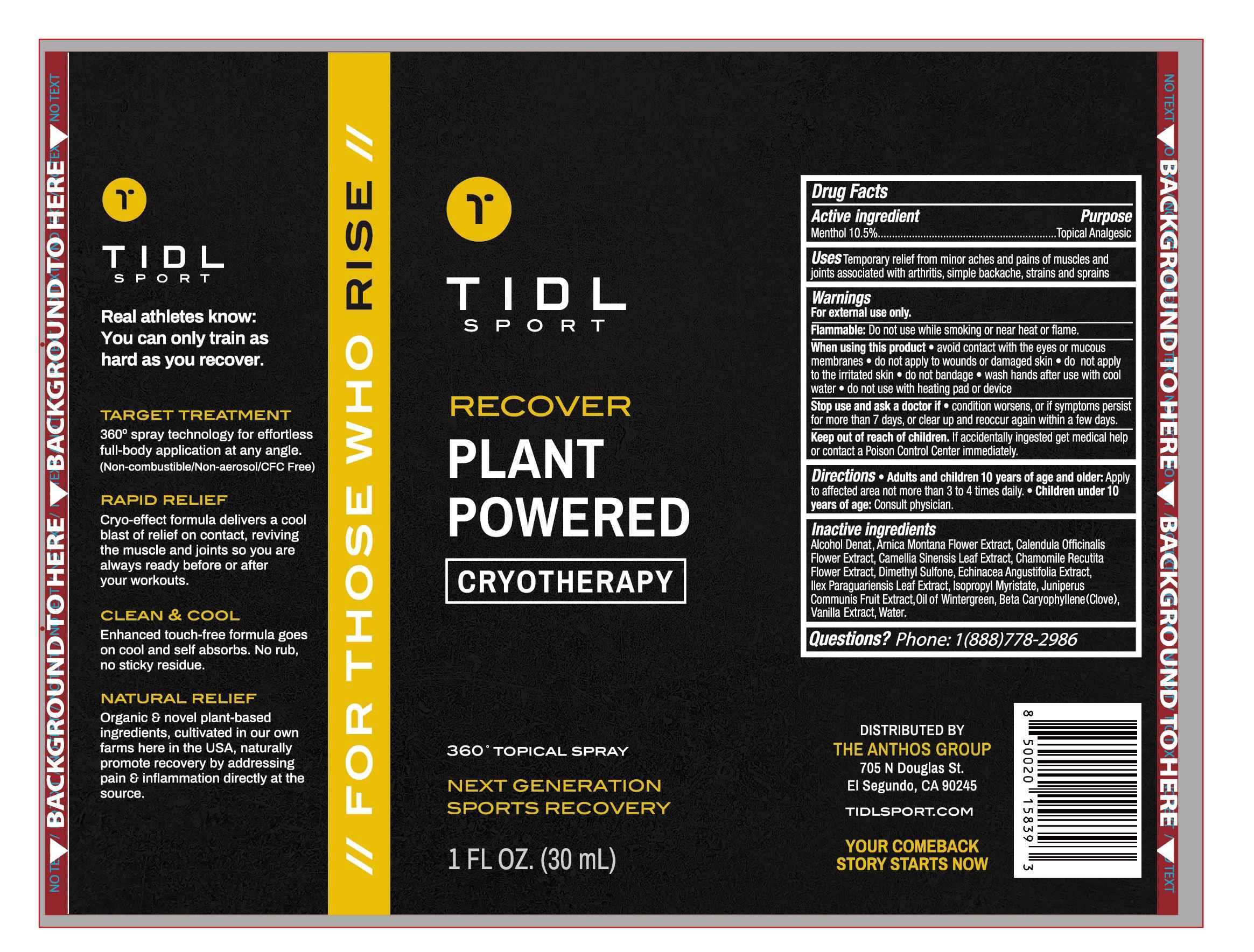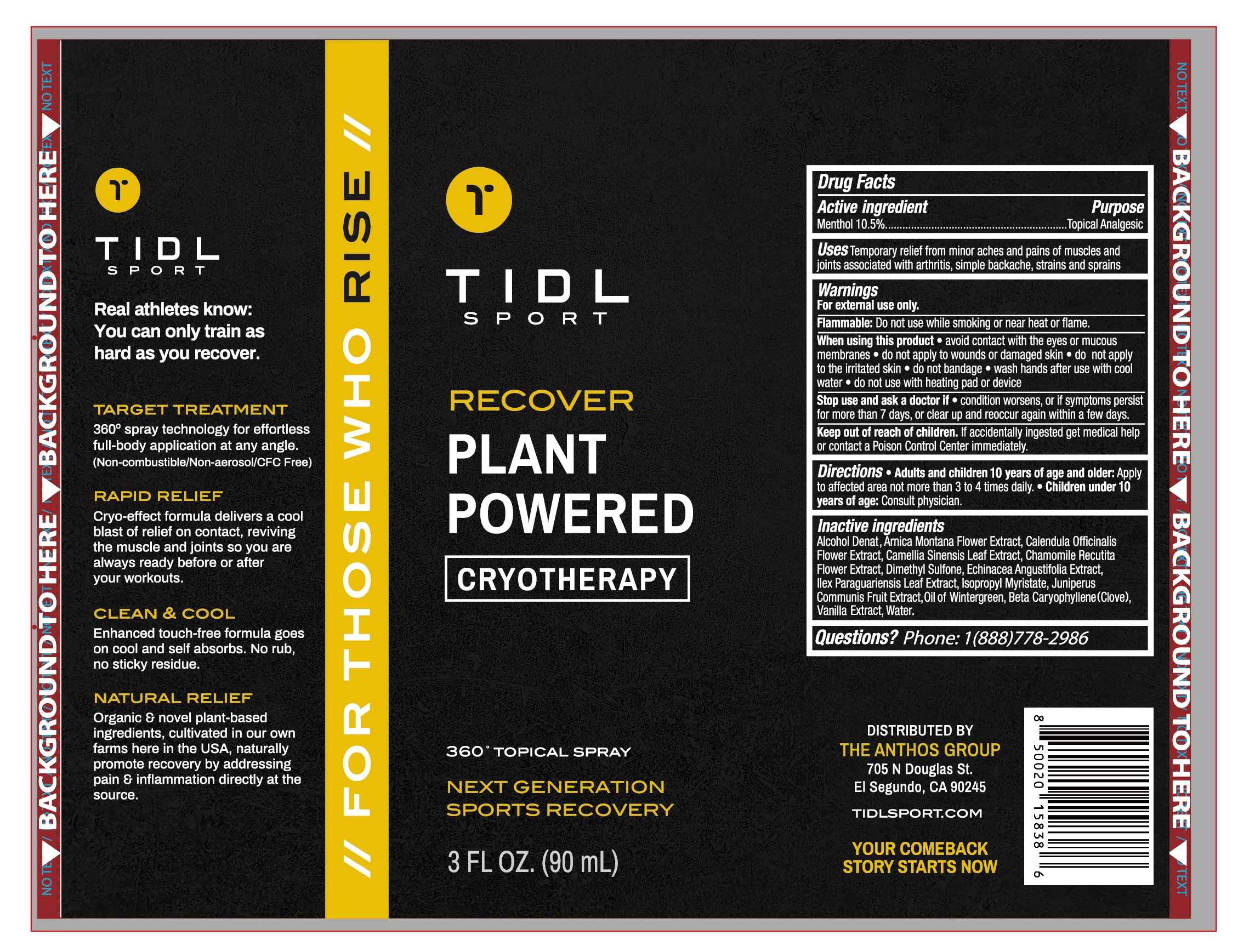 DRUG LABEL: TIDL Sport Plant Powered
NDC: 79740-006 | Form: SPRAY
Manufacturer: ANTHOS GROUP, INC, THE
Category: otc | Type: HUMAN OTC DRUG LABEL
Date: 20230109

ACTIVE INGREDIENTS: MENTHOL 10.5 g/100 mL
INACTIVE INGREDIENTS: METHYL SALICYLATE; VANILLA; ILEX PARAGUARIENSIS LEAF; CARYOPHYLLENE; CHAMOMILE; ALCOHOL; WATER; CALENDULA OFFICINALIS FLOWER; GREEN TEA LEAF; ARNICA MONTANA FLOWER; DIMETHYL SULFONE; ISOPROPYL MYRISTATE; JUNIPER BERRY

79740-006
TIDL Sport Plant Powered Spray

Active Ingredient(s)

Menthol 10.5%

Purpose

Topical Analgesic

Use

Temporary relief from minor aches and pains of muscles and joints associated with art hrt is, simple backache, strains and sprains

Warnings

For external use only.

Flammable：Do not use while smoking or near heat or flame.

When using this product
·avoid contact with the eyes or mucCo US membranes
·do not apply to wounds or damaged skin
·do not appply to the irritated skin
·do not bandage
·wash hands after use wiit hccool water
·do not use with heating pad or device

Stop use and ask a doctor if
·condition worsens, or if symptoms persist for more than 7 days, or clear up and reoccur again within a few days.

Keep out of reach of children.lf accidentally ingested get medical help or contact a Poison Control Center immediately.

Do not use while smoking or near heat or flame.

STOP USE

·condition worsens, or if symptoms persist for more than 7 days, or clear up and reoccur again within a few days.

When using this product
·avoid contact with the eyes or mucCo US membranes
·do not apply to wounds or damaged skin
·do not appply to the irritated skin
·do not bandage
·wash hands after use wiit hccool water
·do not use with heating pad or device

Stop use and ask a doctor if
·condition worsens, or if symptoms persist for more than 7 days, or clear up and reoccur again within a few days.

Keep out of reach of children.lf accidentally ingested get medical help or contact a Poison Control Center immediately.

Keep out of reach of children.lf accidentally ingested get medical help or contact a Poison Control Center immediately.

Directions

Adultsandchildren10yearsofageandolder：Apply to affected area not more than 3 to 4 times daily.·Children un1der 10 years of age：Consult physician.

Other information

/

Inactive ingredients

Alcohol Denat, Arnica Montana Flower Extract, Calendula Officinalis FlowerExtract, Camellia Sinensis Leaf Extract, Chamomile Recutita Flower Extract, Dimethyl Sulfone, Echinacea Angustifolia Extrac, IIex Paragua riennsis LeafExtract, Isopropyl Myristate, Juniperus Communis Fruit Extract, Oil of Wintergreen, Beta Caryophyllene(Clove), Vanilla Extract, Water.

Package Label - Principal Display Panel

79740-006-01 30ml 79740-006-02 90ml